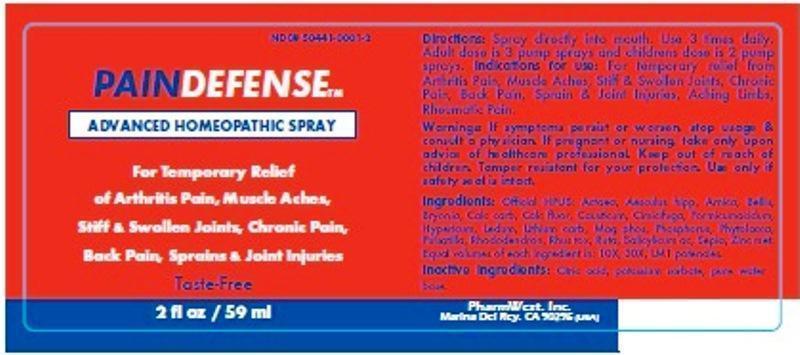 DRUG LABEL: PainDefense
NDC: 50441-0001 | Form: LIQUID
Manufacturer: PharmWest Inc.
Category: homeopathic | Type: HUMAN OTC DRUG LABEL
Date: 20140820

ACTIVE INGREDIENTS: ACTAEA SPICATA ROOT 10 [hp_X]/59 mL; HORSE CHESTNUT 10 [hp_X]/59 mL; ARNICA MONTANA 10 [hp_X]/59 mL; BELLIS PERENNIS 10 [hp_X]/59 mL; BRYONIA ALBA ROOT 10 [hp_X]/59 mL; OYSTER SHELL CALCIUM CARBONATE, CRUDE 10 [hp_X]/59 mL; CALCIUM FLUORIDE 10 [hp_X]/59 mL; CAUSTICUM 10 [hp_X]/59 mL; BLACK COHOSH 10 [hp_X]/59 mL; FORMIC ACID 10 [hp_X]/59 mL; HYPERICUM PERFORATUM 10 [hp_X]/59 mL; LEMNA MINOR 10 [hp_X]/59 mL; LITHIUM CARBONATE 10 [hp_X]/59 mL; MAGNESIUM PHOSPHATE, DIBASIC TRIHYDRATE 10 [hp_X]/59 mL; PHOSPHORUS 10 [hp_X]/59 mL; PHYTOLACCA AMERICANA ROOT 10 [hp_X]/59 mL; PULSATILLA VULGARIS 10 [hp_X]/59 mL; RHODODENDRON AUREUM LEAF 10 [hp_X]/59 mL; TOXICODENDRON PUBESCENS LEAF 10 [hp_X]/59 mL; RUTA GRAVEOLENS FLOWERING TOP 10 [hp_X]/59 mL; SALICYLIC ACID 10 [hp_X]/59 mL; SEPIA OFFICINALIS JUICE 10 [hp_X]/59 mL; ZINC 10 [hp_X]/59 mL
INACTIVE INGREDIENTS: CITRIC ACID MONOHYDRATE; POTASSIUM SORBATE; WATER

PainDefense

ACTIVE INGREDIENT

Active Ingredients: Official HPUS: Actaea spicata, Aesculus hippocastanum, Arnica montana, Bellis perennis, Bryonia, Calcarea carbonica, Calcarea fluorica, Causticum, Cimicifuga racemosa, Formicum acidum, Hypericum perforatum, Lemna minor, Lithium carbonicum, Magnesia phosphorica, Phosphorus, Phytolacca decandra, Pulsatilla, Rhododendron chrysanthum, Rhus toxicodendron, Ruta graveolens, Salicylicum acidum, Sepia, Zincum metallicum. Equal volumes of each ingredient in 10X, 30X, LM1 potencies.

INACTIVE INGREDIENT

Inactive ingredients: Citric acid, potassium sorbate, pure water base.

INDICATIONS AND USAGE

Indications for use: For temporary relief from arthritis pain, muscle aches, stiff and swollen joints, chronic pain, back pain, sprain and joint injuries, aching limbs, rheumatic pain.

DOSAGE AND ADMINISTRATION

Directions: Spray directly into mouth. Use 3 times daily. Adult dose is 3 pump sprays and childrens dose is 2 pump sprays.

WARNINGS

Warnings: If symptoms persist or worsen, stop usage and consult a physician. If pregnant or breast-feeding, take only upon advice of a healthcare professional.

Keep out of the reach of children.

OTHER SAFETY INFORMATION

Tamper resistant for your protection. Use only if safety seal is intact.

PURPOSE

Indications: For temporary relief from:

- arthritis pain
- muscle aches
- stiff and swollen joints
- chronic pain
- back pain
- sprain and joint injuries
- aching limbs
- rheumatic pain